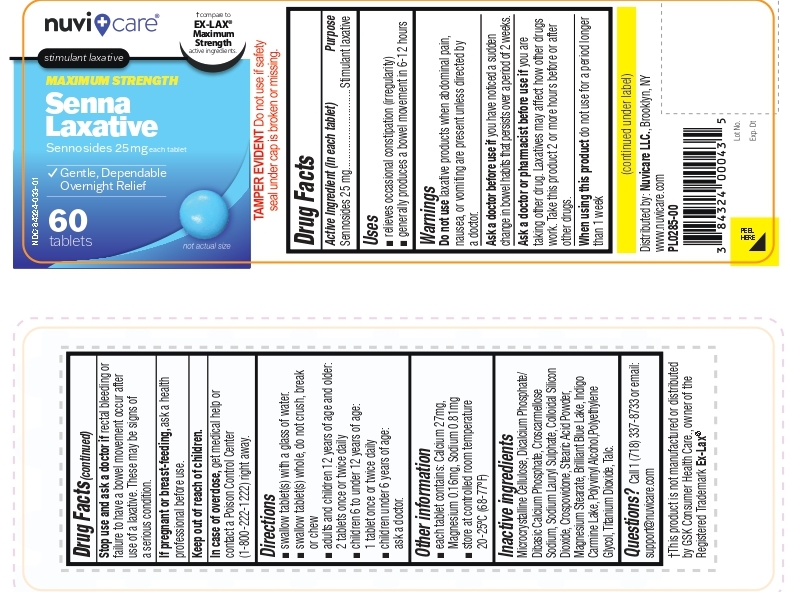 DRUG LABEL: Maximum Strength Senna Laxative
NDC: 84324-033 | Form: TABLET
Manufacturer: NUVICARE LLC
Category: otc | Type: HUMAN OTC DRUG LABEL
Date: 20260122

ACTIVE INGREDIENTS: SENNOSIDES 25 mg/1 1
INACTIVE INGREDIENTS: MICROCRYSTALLINE CELLULOSE; ANHYDROUS DIBASIC CALCIUM PHOSPHATE; CROSCARMELLOSE SODIUM; SODIUM LAURYL SULFATE; SILICON DIOXIDE; CROSPOVIDONE, UNSPECIFIED; STEARIC ACID; MAGNESIUM STEARATE; FD&C BLUE NO. 1; INDIGOTINDISULFONATE SODIUM; POLYVINYL ALCOHOL; POLYETHYLENE GLYCOL, UNSPECIFIED; TITANIUM DIOXIDE; TALC

Active Ingredient (in each tablet)

Sennosides 25 mg

Purpose

Stimulant Laxative

Uses:

- relieves occasional constipation (irregularity).
- generally prodcues a bowel movement in 6-12 hours

Warnings:

Do not use

- laxative products when abdominal pain, nausea, or vomiting are present unless directed by a doctor

Ask a doctor before use if you have

- noticed a sudden change in bowel habits that persists over a period of 2 weeks.

Ask a doctor or pharmacist before use if

- you are taking other drug. Laxatives may affect how other drugs work. Take this product 2 or more hours before or after other drugs.

When using this product

- do not use for a period longer than 1 week

Stop use and ask a doctor if
rectal bleeding or failure to have a bowel movement occur after use of a laxative. These may be signs of a serious condition.

PREGNANCY OR BREAST FEEDING

If pregnant or breast-feeding, ask a health professional before use.

KEEP OUT OF REACH OF CHILDREN. In case of overdose, get medical help or contact a Poison Control Center (1-800-222-1222) right away.

DIRECTIONS

- swallow tablet (s) with a glass of water.
- swallow tablet (s) whole, do not crush, break or chew.
- adults and children 12 years of age and older: 2 tablets once or twice daily
- children 6 to under 12 years of age: 1 tablet once or twice daily
- children under 6 years of age: ask a doctor

OTHER INFORMATION

- each tablet contains: Calcium 27 mg, Magnesium 0.16 mg, Sodium 0.81 mg
- store at controlled room temperature 20-25°C (68-77°F)

INACTIVE INGREDIENTS

Microcrystalline Cellulose, Dicalcium Phosphate/Dibasic Calcium Phosphate, Croscarmellose Sodium, Sodium Lauryl sulphate, Colloidal Silicon Dioxide, Crospovidone, Stearic acid powder, Magnesium Stearate, Brilliant Blue Lake, Indigo Carmine Lake, Polyvinly Alcohol, Polyethylene Glycol, Titanium Dioxide, Talc

QUESTIONS OR COMMENTS?

Call 1 (718) 337-8733 or email: support@nuvicare.com